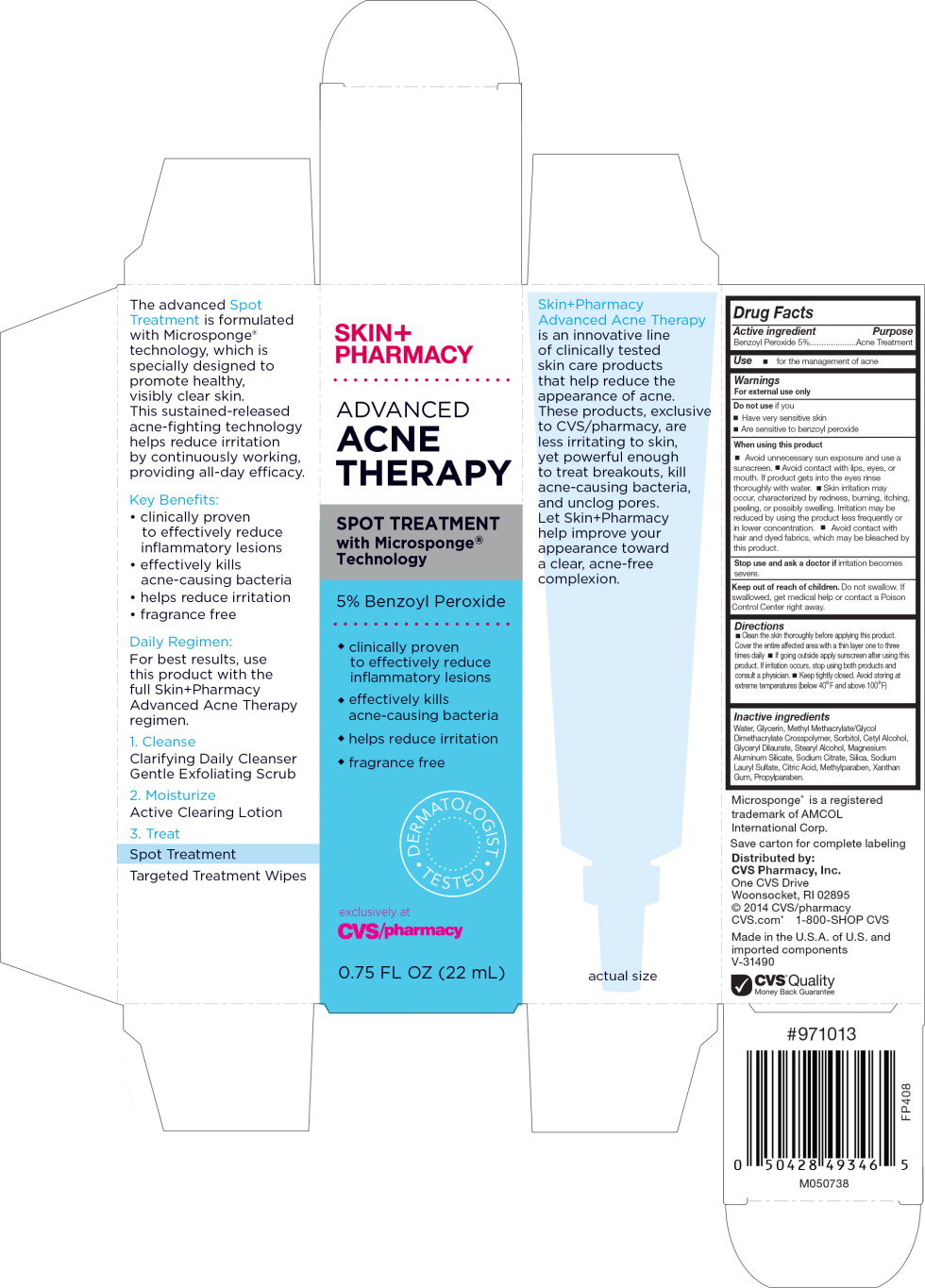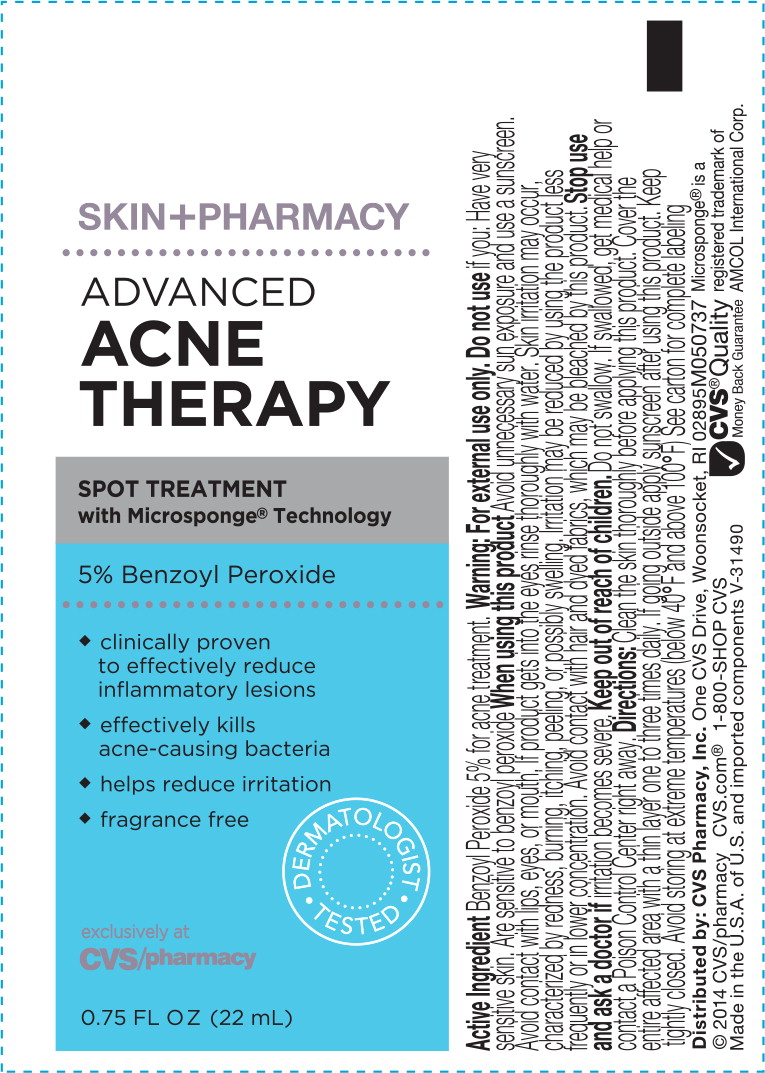 DRUG LABEL: SkinPharmacy Advanced Acne Therapy Spot Treatment
NDC: 69842-023 | Form: LIQUID
Manufacturer: CVS Health
Category: otc | Type: HUMAN OTC DRUG LABEL
Date: 20170328

ACTIVE INGREDIENTS: benzoyl peroxide 50 mg/1 mL
INACTIVE INGREDIENTS: water; glycerin; methyl methacrylate/glycol dimethacrylate crosspolymer; cetyl alcohol; sorbitol; glyceryl dilaurate; stearyl alcohol; magnesium aluminum silicate; sodium citrate; silicon dioxide; sodium lauryl sulfate; citric acid monohydrate; methylparaben; xanthan gum; propylparaben

Drug Facts

Active Ingredient

Benzoyl Peroxide 5%

Purpose

Acne Treatment

Use

- for the management of acne

Warnings

For external use only

Do not this medication if you

- Have very sensitive skin
- Are sensitive to benzoyl peroxide

When using this product

- Avoid unnecessary sun exposure and use a sunscreen.
- Avoid contact with lips, eyes, or mouth. If product gets into the rinse thoroughly with water.
- Skin irritation may occur, characterized by redness, burning, itching, peeling, or possible swelling. Irritation may be reduced by using the product less frequently or in lower concentration.
- Avoid contact with hair and dyed fabrics, which may be bleached by this product.

Stop use and ask a doctor if irritation becomes severe.

Keep out of reach of children. Do not swallow. If swallowed, get medical help or contact a Poison Control Center right away.

Directions

- Clean skin thoroughly before applying this product. Cover the entire affected area with a thin layer one to three times daily.
- If going outside apply sunscreen after using this product. If irritation occurs, stop using both products and consult a physician.
- Keep tightly closed Avoid storing at extreme temperature (below 40°F and above 100°F)

Inactive ingredients

Water, Glycerin, Methyl Methacrylate/Glycol Dimethacrylate Crosspolymer, Sorbitol, Cetyl Alcohol, Glyceryl Dilaurate, Stearyl Alcohol, Magnesium Aluminum Silicate, Sodium Citrate, Silica, Sodium Lauryl Sulfate, Citric Acid, Methylparaben, Xanthan Gum, Propylparaben.

Microsponge® is a registered trademark of AMCOL International Corp.

Save carton for complete labeling

Distributed by: CVS Pharmacy, Inc.

One CVS Drive, Woonsocket, RI 02895

© 2014 CVS/pharmacy

CVS.com® 1-800-SHOP CVS

Made in the U.S.A. of U.S. and imported components

V-31490

CVS® Quality

Money Back Guarantee

#971013

M050738

FP408

Principal Display Panel - Carton Label

SKIN+
PHARMACY

ADVANCED
ACNE
THERAPY

SPOT TREATMENT
with Microsponge® Technology

5% Benzoyl Peroxide

- clinically proven
  to effectively reduce
  inflammatory lesions
- effectively kills
  acne-causing bacteria
- helps reduce irritation
- fragrance free

DERMATOLOGIST TESTED

exclusively at
CVS/pharmacy

0.75 FL OZ (22 mL)

Principal Display Panel - Label

SKIN+PHARMACY

ADVANCED
ACNE
THERAPY

SPOT TREATMENT
with Microsponge® Technology

5% Benzoyl Peroxide

- clinically proven
  to effectively reduce
  inflammatory lesions
- effectively kills
  acne-causing bacteria
- helps reduce irritation
- fragrance free

DERMATOLOGIST TESTED

exclusively at
CVS/pharmacy

0.75 FL OZ (22 mL)